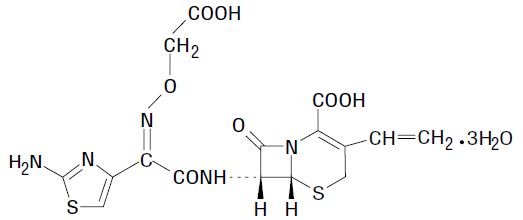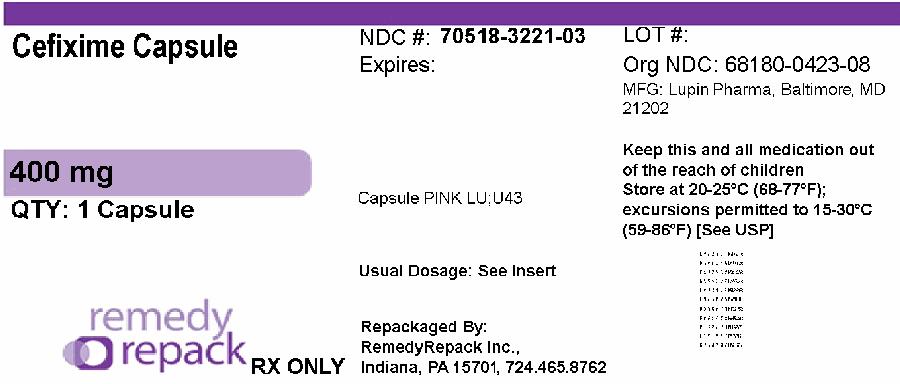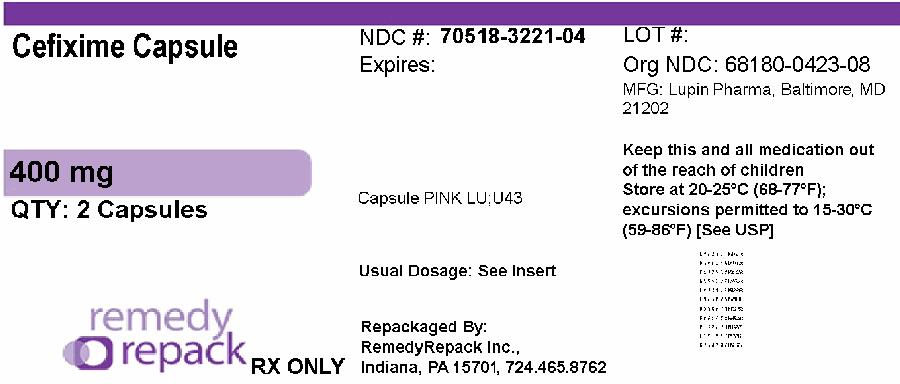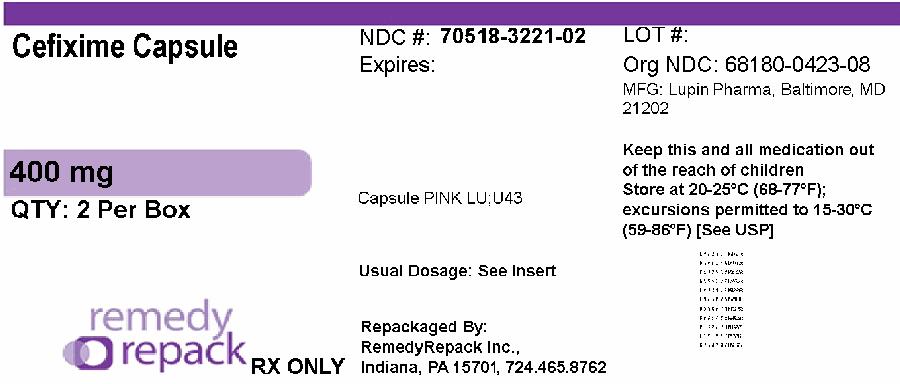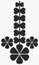 DRUG LABEL: CEFIXIME
NDC: 70518-3221 | Form: CAPSULE
Manufacturer: REMEDYREPACK INC.
Category: prescription | Type: HUMAN PRESCRIPTION DRUG LABEL
Date: 20251201

ACTIVE INGREDIENTS: CEFIXIME 400 mg/1 1
INACTIVE INGREDIENTS: CROSCARMELLOSE SODIUM; FERRIC OXIDE RED; FERROSOFERRIC OXIDE; GELATIN; HYDROXYPROPYL CELLULOSE, LOW SUBSTITUTED; MAGNESIUM STEARATE; MANNITOL; POTASSIUM HYDROXIDE; PROPYLENE GLYCOL; SHELLAC; SILICON DIOXIDE; SODIUM LAURYL SULFATE; TITANIUM DIOXIDE

HIGHLIGHTS OF PRESCRIBING INFORMATION

These highlights do not include all the information needed to use CEFIXIME safely and effectively. See full prescribing information for CEFIXIME.
CEFIXIME for oral suspension, 100 mg/5 mL
CEFIXIME for oral suspension, 200 mg/5 mL
CEFIXIME capsules, 400 mg
For oral administration
Initial U.S. Approval: 1986

1 INDICATIONS AND USAGE

Cefixime is a cephalosporin antibacterial drug indicated in the treatment of adults and pediatric patients six months and older with the following infections:

- Uncomplicated Urinary Tract Infections (1.1)
- Otitis Media (1.2)
- Pharyngitis and Tonsillitis (1.3)
- Acute Exacerbations of Chronic Bronchitis (1.4)
- Uncomplicated Gonorrhea (cervical/urethral) (1.5)

Usage to Reduce Development of Drug-Resistant Bacteria

To reduce the development of drug-resistant bacteria and maintain the effectiveness of cefixime and other antibacterial drugs, cefixime for oral suspension and cefixime capsules should be used only to treat infections that are proven or strongly suspected to be caused by bacteria. (1.6)

2 DOSAGE AND ADMINISTRATION

- Adults: 400 mg daily (2.1)
- Pediatric patients (6 months and older): 8 mg/kg/day (2.2)

3 DOSAGE FORMS AND STRENGTHS

- Oral Suspension: 100 mg/5 mL and 200 mg/5 mL (3)
- Capsules: 400mg (3)

4 CONTRAINDICATIONS

- Contraindicated in patients with known allergy to cefixime or other cephalosporins. (4)

5 WARNINGS AND PRECAUTIONS

- Hypersensitivity reactions including shock and fatalities have been reported with cefixime. Discontinue use if a reaction occurs. (5.1)
- Clostridiodes difficile-Associated Diarrhea: Evaluate if diarrhea occurs. (5.2)

6 ADVERSE REACTIONS

Most common adverse reactions are gastrointestinal such as diarrhea (16%), nausea (7%), loose stools (6%), abdominal pain (3%), dyspepsia (3%), and vomiting. (6)

To report SUSPECTED ADVERSE REACTIONS, contact Lupin Pharmaceuticals, Inc. at 1-800-399-2561 or FDA at 1-800-FDA-1088 or www.fda.gov/medwatch.

7 DRUG INTERACTIONS

- Elevated carbamazepine levels have been reported in postmarketing experience when cefixime is administered concomitantly. (7.1)
- Increased prothrombin time, with or without clinical bleeding, has been reported when cefixime is administered concomitantly with warfarin and anticoagulants. (7.2)

8 USE IN SPECIFIC POPULATIONS

- Pediatric Use: Efficacy and safety in pediatric patients younger than 6 months of age have not been established. (8.4)
- Geriatric Use: Clinical studies did not include sufficient numbers of subjects aged 65 and older to determine whether they respond differently than younger subjects. Other reported clinical experience has not identified differences in responses between the elderly and younger patients. (8.5)
- Renal Impairment: Cefixime may be administered in the presence of impaired renal function. Dose adjustment is required in patients whose creatinine clearance is less than 60 mL/min. (8.6)

FULL PRESCRIBING INFORMATION

1 INDICATIONS AND USAGE

1.1 Uncomplicated Urinary Tract Infections

Cefixime for oral suspension and cefixime capsule is indicated in the treatment of adults and pediatric patients six months of age or older with uncomplicated urinary tract infections caused by susceptible isolates of Escherichia coliand Proteus mirabilis.

1.2 Otitis Media

Cefixime for oral suspension and cefixime capsule is indicated in the treatment of adults and pediatric patients six months of age or older with otitis media caused by susceptible isolates of Haemophilus influenzae, Moraxella catarrhalis, and Streptococcus pyogenes. (Efficacy for Streptococcus pyogenesin this organ system was studied in fewer than 10 infections.)

Note: For patients with otitis media caused by Streptococcus pneumoniae, overall response was approximately 10% lower for cefixime than for the comparator [see Clinical Studies (14)] .

1.3 Pharyngitis and Tonsillitis

Cefixime for oral suspension and cefixime capsule is indicated in the treatment of adults and pediatric patients six months of age or older with pharyngitis and tonsillitis caused by susceptible isolates of Streptococcus pyogenes. (Note: Penicillin is the usual drug of choice in the treatment of Streptococcus pyogenesinfections. Cefixime for oral suspension and cefixime capsule is generally effective in the eradication of Streptococcus pyogenesfrom the nasopharynx; however, data establishing the efficacy of cefixime for oral suspension and cefixime capsule in the subsequent prevention of rheumatic fever is not available.)

1.4 Acute Exacerbations of Chronic Bronchitis

Cefixime for oral suspension and cefixime capsule is indicated in the treatment of adults and pediatric patients six months of age or older with acute exacerbations of chronic bronchitis caused by susceptible isolates of Streptococcus pneumoniaeand Haemophilus influenzae.

1.5 Uncomplicated Gonorrhea (cervical/urethral)

Cefixime for oral suspension and cefixime capsule is indicated in the treatment of adults and pediatric patients six months of age or older with uncomplicated gonorrhea (cervical/urethral) caused by susceptible isolates of Neisseria gonorrhoeae(penicillinase-and non-penicillinase-producing isolates).

1.6 Usage to Reduce Development of Drug-Resistant Bacteria

To reduce the development of drug resistant bacteria and maintain the effectiveness of cefixime and other antibacterial drugs, cefixime for oral suspension and cefixime capsule should be used only to treat infections that are proven or strongly suspected to be caused by susceptible bacteria. When culture and susceptibility information are available, they should be considered in selecting or modifying antimicrobial therapy. In the absence of such data, local epidemiology and susceptibility patterns may contribute to the empiric selection of therapy.

2 DOSAGE AND ADMINISTRATION

2.1 Adults

The recommended dose of cefixime is 400 mg daily. This may be given as a 400 mg capsule daily. For the treatment of uncomplicated cervical/urethral gonococcal infections, a single oral dose of 400 mg is recommended. The capsule may be administered without regard to food.

In the treatment of infections due to Streptococcus pyogenes, a therapeutic dosage of cefixime should be administered for at least 10 days.

2.2 Pediatric Patients (6 months or older)

The recommended dose is 8 mg/kg/day of the cefixime for suspension. This may be administered as a single daily dose or may be given in two divided doses, as 4 mg/kg every 12 hours.

Note: A suggested dose has been determined for each pediatric weight range. Refer to Table 1. Ensure all orders that specify a dose in milliliters include a concentration, because cefixime for oral suspension is available in two different concentrations (100 mg/5 mL and 200 mg/5 mL).

Table1. Suggested doses for pediatric patients
PEDIATRICDOSAGECHART
Doses are suggested for each weight range and rounded for ease of administration
 |  | Cefiximefor oralsuspension
 |  | 100 mg/5 mL | 200 mg/5 mL
Patient Weight (kg) | Dose/Day (mg) | Dose/Day (mL) | Dose/Day (mL)
5 to 7.5 | 50 | 2.5 | --
7.6 to 10 | 80 | 4 | 2
10.1 to 12.5 | 100 | 5 | 2.5
12.6 to 20.5 | 150 | 7.5 | 4
20.6 to 28 | 200 | 10 | 5
28.1 to 33 | 250 | 12.5 | 6
33.1 to 40 | 300 | 15 | 7.5
40.1 to 45 | 350 | 17.5 | 9
45.1 or greater | 400 | 20 | 10

Pediatric patients weighing more than 45 kg or older than 12 years should be treated with the recommended adult dose.

Otitis media should be treated with cefixime for oral suspension. Clinical trials of otitis media were conducted with the suspension, and the suspension results in higher peak blood levels than the tablet when administered at the same dose.

Therefore, the cefixime tablet or cefixime capsule should not be substituted for the cefixime for oral suspension in the treatment of otitis media [see Clinical Pharmacology (12.3)].

In the treatment of infections due to Streptococcus pyogenes, a therapeutic dosage of cefixime should be administered for at least 10 days.

2.3 Renal Impairment

Cefixime may be administered in the presence of impaired renal function. Normal dose and schedule may be employed in patients with creatinine clearances of 60 mL/min or greater. Refer to Table 2 for dose adjustments for adults with renal impairment. Neither hemodialysis nor peritoneal dialysis removes significant amounts of drug from the body.

Table2. Doses for Adults with Renal Impairment
Renal Dysfunction | Cefiximefor Oral Suspension
Creatinine Clearance (mL/min) | 100 mg/5 mL | 200 mg/5 mL
 | Dose/Day (mL) | Dose/Day (mL)
60 or greater | Normal dose | Normal dose
21 to 59* OR renal hemodialysis* | 13 | 6.5
20 or less OR continuous peritoneal dialysis | 8.6 | 4.4
*The preferred concentrations of oral suspension to use are 200 mg/5 mL for patients with this renal dysfunction

2.4 Reconstitution Directions for Cefixime for Oral Suspension

Table 3. Reconstitution Direction for Cefixime for Oral Suspension
Strength | Bottle Size | Reconstitution Directions
200 mg/5 mL | 75 mL | To reconstitute, suspend with 51 mLwater. Method: Tap the bottle several times to loosen powder contents prior to reconstitution. Add approximately half the total amount of water for reconstitution and shake well. Add the remainder of water and shake well.
100 mg/5 mL and 200 mg/5 mL | 50 mL | To reconstitute, suspend with 34 mLwater. Method: Tap the bottle several times to loosen powder contents prior to reconstitution. Add approximately half the total amount of water for reconstitution and shake well. Add the remainder of water and shake well.

After reconstitution, the suspension may be kept for 14 days either at room temperature, or under refrigeration, without significant loss of potency. Keep tightly closed. Shake well before using. Discard unused portion after 14 days.

3 DOSAGE FORMS AND STRENGTHS

Cefixime capsule is available for oral administration as capsules which provide 400 mg of cefixime as trihydrate. These are size "0" capsules with pink opaque cap and pink opaque body, imprinted with "LU" on the cap and "U43" on the body in black ink. Capsules contain white to yellowish white granular powder.

4 CONTRAINDICATIONS

Cefixime is contraindicated in patients with known allergy to cefixime or other cephalosporins.

5 WARNINGS AND PRECAUTIONS

5.1 Hypersensitivity Reactions

Anaphylactic/anaphylactoid reactions (including shock and fatalities) have been reported with the use of cefixime.

Before therapy with cefixime is instituted, careful inquiry should be made to determine whether the patient has had previous hypersensitivity reactions to cephalosporins, penicillins, or other drugs. If this product is to be given to penicillin-sensitive patients, caution should be exercised because cross hypersensitivity among beta-lactam antibacterial drugs has been clearly documented and may occur in up to 10% of patients with a history of penicillin allergy. If an allergic reaction to cefixime occurs, discontinue the drug.

5.2 Clostridioides difficile-Associated Diarrhea

Clostridium difficile-associated diarrhea (CDAD) has been reported with use of nearly all antibacterial agents, including cefixime, and may range in severity from mild diarrhea to fatal colitis. Treatment with antibacterial agents alters the normal flora of the colon leading to overgrowth of C. difficile.

C. difficileproduces toxins A and B which contribute to the development of CDAD. Hypertoxin producing isolates of C. difficilecause increased morbidity and mortality, as these infections can be refractory to antimicrobial therapy and may require colectomy. CDAD must be considered in all patients who present with diarrhea following antibacterial drug use. Careful medical history is necessary since CDAD has been reported to occur over two months after the administration of antibacterial agents.

If CDAD is suspected or confirmed, ongoing antibacterial drug use not directed against C. difficilemay need to be discontinued. Appropriate fluid and electrolyte management, protein supplementation, antibacterial drug treatment of C. difficile,and surgical evaluation should be instituted as clinically indicated.

5.3 Dose Adjustment in Renal Impairment

The dose of cefixime should be adjusted in patients with renal impairment as well as those undergoing continuous ambulatory peritoneal dialysis (CAPD) and hemodialysis (HD). Patients on dialysis should be monitored carefully [see Dosage and Administration (2)] .

5.4 Coagulation Effects

Cephalosporins, including cefixime, may be associated with a fall in prothrombin activity. Those at risk include patients with renal or hepatic impairment, or poor nutritional state, as well as patients receiving a protracted course of antimicrobial therapy, and patients previously stabilized on anticoagulant therapy. Prothrombin time should be monitored in patients at risk and exogenous vitamin K administered as indicated.

5.5 Development of Drug-Resistant Bacteria

Prescribing cefixime in the absence of a proven or strongly suspected bacterial infection is unlikely to provide benefit to the patient and increases the risk of the development of drug-resistant bacteria.

6 ADVERSE REACTIONS

6.1 Clinical Trials Experience

Because clinical trials are conducted under widely varying conditions, adverse reaction rates observed in the clinical trials of a drug cannot be directly compared to rates in the clinical trials of another drug and may not reflect the rates observed in practice.

The most commonly seen adverse reactions in U.S. trials of the tablet formulation were gastrointestinal events, which were reported in 30% of adult patients on either the twice daily or the once daily regimen. Five percent (5%) of patients in the U.S. clinical trials discontinued therapy because of drug-related adverse reactions. Individual adverse reactions included diarrhea 16%, loose or frequent stools 6%, abdominal pain 3%, nausea 7%, dyspepsia 3%, and flatulence 4%. The incidence of gastrointestinal adverse reactions, including diarrhea and loose stools, in pediatric patients receiving the suspension was comparable to the incidence seen in adult patients receiving tablets.

6.2 Post-marketing Experience

The following adverse reactions have been reported following the post-approval use of cefixime. Incidence rates were less than 1 in 50 (less than 2%).

Gastrointestinal

Several cases of documented pseudomembranous colitis were identified in clinical trials. The onset of pseudomembranous colitis symptoms may occur during or after therapy.

Hypersensitivity Reactions

Anaphylactic/anaphylactoid reactions (including shock and fatalities), skin rashes, urticaria, drug fever, pruritus, angioedema, and facial edema. Erythema multiforme, Stevens-Johnson syndrome, and serum sickness-like reactions have been reported.

Hepatic

Transient elevations in SGPT, SGOT, alkaline phosphatase, hepatitis, jaundice.

Renal

Transient elevations in BUN or creatinine, acute renal failure.

Central Nervous System

Headaches, dizziness, seizures.

Hemic and Lymphatic System

Transient thrombocytopenia, leukopenia, neutropenia, prolongation in prothrombin time, elevated LDH, pancytopenia, agranulocytosis, and eosinophilia.

Abnormal Laboratory Tests

Hyperbilirubinemia.

Other Adverse Reactions

Genital pruritus, vaginitis, candidiasis, toxic epidermal necrolysis.

Adverse Reactions Reported for Cephalosporin-class Drugs

Allergic reactions, superinfection, renal dysfunction, toxic nephropathy, hepatic dysfunction including cholestasis, aplastic anemia, hemolytic anemia, hemorrhage, and colitis.

Several cephalosporins have been implicated in triggering seizures, particularly in patients with renal impairment when the dosage was not reduced [see Dosage and Administration (2) and Overdosage (10)] . If seizures associated with drug therapy occur, the drug should be discontinued. Anticonvulsant therapy can be given if clinically indicated.

7 DRUG INTERACTIONS

7.1 Carbamazepine

Elevated carbamazepine levels have been reported in postmarketing experience when cefixime is administered concomitantly. Drug monitoring may be of assistance in detecting alterations in carbamazepine plasma concentrations.

7.2 Warfarin and Anticoagulants

Increased prothrombin time, with or without clinical bleeding, has been reported when cefixime is administered concomitantly.

7.3 Drug/Laboratory Test Interactions

A false-positive reaction for ketones in the urine may occur with tests using nitroprusside but not with those using nitroferricyanide.

The administration of cefixime may result in a false positive reaction for glucose in the urine when using glucose tests based on the Benedict's solution or Fehling's solution. It is recommended that glucose tests based on enzymatic glucose oxidase reactions be used. A false positive direct Coombs test has been reported during treatment with other cephalosporins; therefore, it should be recognized that a positive Coombs test may be due to the drug.

8 USE IN SPECIFIC POPULATIONS

8.1 Pregnancy

Risk Summary

Available data from published observational studies, case series, and case reports over several decades with cephalosporin use, including cefixime, in pregnant women have not established drug-associated risks of major birth defects, miscarriage, or adverse maternal or fetal outcomes (see Data). Reproduction studies have been performed in mice and rats at doses equivalent to 40 and 80 times, respectively, the adult human recommended dose and have revealed no evidence of harm to the fetus due to cefixime (see Data).

The background risk of major birth defects and miscarriage for the indicated population is unknown. All pregnancies have a background risk of birth defect, loss, or other adverse outcomes. In the U.S. general population, the estimated background risks of major birth defects and miscarriage in clinically recognized pregnancies is 2% to 4% and 15% to 20%, respectively.

Clinical Considerations

Disease-Associated Maternal and/or Embryo/Fetal Risk

Maternal gonorrhea may be associated with preterm birth, low neonatal birth weight, chorioamnionitis, intrauterine growth restriction, small for gestational age and premature rupture of membranes. Perinatal transmission of gonorrhea to the offspring can result in infant blindness, joint infections, and bloodstream infections.

Data

Human Data

While available studies cannot definitively establish the absence of risk, published data from prospective cohort studies, case series, and case reports over several decades have not identified a consistent association with cephalosporin use, including cefixime, during pregnancy, and major birth defects, miscarriage, or other adverse maternal or fetal outcomes. Available studies have methodological limitations, including small sample size, retrospective data collection, and inconsistent comparator groups.

Animal Data

The results of embryo-fetal development studies in mice and rats show that cefixime, at doses up to 3200 mg/kg/day administered during the period of organogenesis did not adversely affect development. In these studies, in mice and rats, cefixime did not affect postnatal development or reproductive capacity of the F1generation or fetal development of the F2generation. In an embryo-fetal development study in rabbits, cefixime at doses of 3.2, 10 or 32 mg/kg given daily during the period of organogenesis (gestation days 6 through 18) resulted in abortions and/or maternal deaths at doses > 10 mg/kg (typically associated with the administration of antibiotics in this species), but no malformations were reported at lower doses. A pre- and post-natal development study of cefixime at oral doses up to 3200 mg/kg/day in rats demonstrated no effect on the duration of pregnancy, process of parturition, development and viability of offspring, or reproductive capacity of the F1generation and development of their fetuses (F2).

8.2 Lactation

Risk Summary

There are no available data on the presence of cefixime in human milk, the effects on the breast-fed infant, or the effects on milk production. Cefixime is present in animal milk (see Data). When a drug is present in animal milk, it is likely the drug will be present in human milk. The developmental and health benefits of breastfeeding should be considered along with the mother's clinical need for cefixime and any potential adverse effects on the breast-fed infant from cefixime or from the mother's underlying condition.

Data

In a study on disposition of cefixime in pregnant and lactating rats, continuous intra-peritoneal infusion of 2.54 mg/kg/day of^14C-cefixime from days 10 to 14 postpartum resulted in steady state plasma concentrations of radioactivity in the dams that were 70 times greater than in their nursing pups.

After 102 hours of drug infusion, total radioactivity in the body of the pups, including the stomach and intestinal contents, was 1.5% of the^14C-cefixime estimated to be in the mother's body at steady state.^1

8.4 Pediatric Use

The safety and effectiveness of cefixime have been established in pediatric patients 6 months of age and older. Safety and effectiveness of cefixime in pediatric patients younger than 6 months of age have not been established. The incidence of gastrointestinal adverse reactions, including diarrhea and loose stools, in the pediatric patients receiving the cefixime for oral suspension, was comparable to the incidence seen in adult patients receiving tablets.

8.5 Geriatric Use

Clinical studies did not include sufficient numbers of subjects aged 65 and older to determine whether they respond differently than younger subjects. Other reported clinical experience has not identified differences in responses between the elderly and younger patients. A pharmacokinetic study in the elderly detected differences in pharmacokinetic parameters [see Clinical Pharmacology (12.3)] . These differences were small and do not indicate a need for dosage adjustment of cefixime in the elderly.

8.6 Renal Impairment

The dose of cefixime should be adjusted in patients with renal impairment as well as those undergoing continuous ambulatory peritoneal dialysis (CAPD) and hemodialysis (HD). Patients on dialysis should be monitored carefully [see Dosage and Administration (2.3)] .

10 OVERDOSAGE

Gastric lavage may be indicated; otherwise, no specific antidote exists. Cefixime is not removed in significant quantities from the circulation by hemodialysis or peritoneal dialysis. Adverse reactions in small numbers of healthy adult volunteers receiving single doses up to 2 g of cefixime did not differ from the profile seen in patients treated at the recommended doses.

11 DESCRIPTION

Cefixime is a semisynthetic, cephalosporin antibacterial for oral administration. Chemically, it is (6R, 7R)-7-[2-(2-Amino-4-thiazolyl)glyoxylamido]-8-oxo-3-vinyl-5-thia-1-azabicyclo [4.2.0] oct-2-ene-2-carboxylic acid, 7^2-(Z)-[ O-(carboxy methyl) oxime] trihydrate.

Molecular weight = 507.50 as the trihydrate. Chemical Formula is C16H15N5O7S2.3H2O

The structural formula for cefixime is:

Inactive ingredients contained in the cefixime powder for oral suspension USP are colloidal silicon dioxide, sodium benzoate, strawberry flavor, sucrose, and xanthan gum.

Inactive ingredients contained in the cefixime capsules 400 mg are colloidal silicon dioxide, croscarmellose sodium, low substituted hydroxy propyl cellulose, magnesium stearate, and mannitol. The capsule shell contains the following inactive ingredients: ferric oxide black, ferric oxide red, gelatin, potassium hydroxide, propylene glycol, shellac, sodium lauryl sulfate, and titanium dioxide.

12 CLINICAL PHARMACOLOGY

12.1 Mechanism of Action

Cefixime is a semisynthetic cephalosporin antibacterial drug [see Microbiology (12.4)] .

12.3 Pharmacokinetics

Cefixime tablets and cefixime for oral suspension, given orally, are about 40% to 50% absorbed whether administered with or without food; however, time to maximal absorption is increased approximately 0.8 hours when administered with food. A single 200 mg tablet of cefixime produces an average peak serum concentration of approximately 2 mcg/mL (range 1 to 4 mcg/mL); a single 400 mg tablet produces an average peak concentration of approximately 3.7 mcg/mL (range 1.3 to 7.7 mcg/mL). The cefixime oral suspension produces average peak concentrations approximately 25% to 50% higher than the tablets, when tested in normal adultvolunteers. Two hundred and 400 mg doses of cefixime oral suspension produce average peak concentrations of 3 mcg/mL (range 1 to 4.5 mcg/mL) and 4.6 mcg/mL (range 1.9 to 7.7 mcg/mL), respectively, when tested in normal adultvolunteers. The area under the time versus concentration curve (AUC) is greater by approximately 10% to 25% with the cefixime for oral suspension than with the tablet after doses of 100 to 400 mg, when tested in normal adultvolunteers. This increased absorption should be taken into consideration if the cefixime for oral suspension is to be substituted for the tablet. Because of the lack of bioequivalence, cefixime tablets should not be substituted for cefixime for oral suspension in the treatment of otitis media [see Dosage and Administration (2)] . Cross-over studies of tablet versus suspension have not been performed in children.

The 400 mg cefixime capsule is bioequivalent to the 400 mg cefixime tablet under fasting conditions. However, food reduces the absorption following administration of the capsule by approximately 15% based on AUC and 25% based on Cmax.

Peak serum concentrations occur between 2 and 6 hours following oral administration of a single 200 mg tablet, a single 400 mg cefixime tablet or 400 mg of cefixime for oral suspension. Peak serum concentrations occur between 2 and 5 hours following a single administration of 200 mg of cefixime for oral suspension. Peak serum concentrations occur between 3 and 8 hours following oral administration of a single 400 mg cefixime capsule.

Distribution

Serum protein binding is concentration independent with a bound fraction of approximately 65%. In a multiple dose study conducted with a research formulation which is less bioavailable than the cefixime tablet or cefixime for oral suspension, there was little accumulation of drug in serum or urine after dosing for 14 days. Adequate data on CSF levels of cefixime are not available.

Elimination

Metabolism and Excretion

There is no evidence of metabolism of cefixime in vivo.Approximately 50% of the absorbed dose is excreted unchanged in the urine in 24 hours. In animal studies, it was noted that cefixime is also excreted in the bile in excess of 10% of the administered dose. The serum half-life of cefixime in healthy subjects is independent of dosage form and averages 3 to 4 hours but may range up to 9 hours in some normal volunteers.

Specific Populations

Geriatric Patients :Average AUCs at steady state in elderly patients are approximately 40% higher than average AUCs in other healthy adults. Differences in the pharmacokinetic parameters between 12 young and 12 elderly subjects who received 400 mg of cefixime once daily for 5 days are summarized as follows:

Table 4. Pharmacokinetic Parameters for Cefixime in Both Young and Elderly Subjects
Pharmacokinetic Parameters (mean±SD) for Cefiximein Both Young&Elderly Subjects
Pharmacokineticparameter | Young | Elderly
Cmax(mg/L) | 4.74 ± 1.43 | 5.68 ± 1.83
Tmax(h)* | 3.9 ± 0.3 | 4.3 ± 0.6
AUC (mg.h/L)* | 34.9 ± 12.2 | 49.5 ± 19.1
T½(h)* | 3.5 ± 0.6 | 4.2 ± 0.4
Cave(mg/L)* | 1.42 ±0.50 | 1.99 ± 0.75
*Difference between age groups was significant. (p<0.05)

However, these increases were not clinically significant [see Dosage and Administration (2)] .

Patients with Renal Impairment:In subjects with moderate impairment of renal function (20 to 40 mL/min creatinine clearance), the average serum half-life of cefixime is prolonged to 6.4 hours. In severe renal impairment (5 to 20 mL/min creatinine clearance), the half-life increased to an average of 11.5 hours. The drug is not cleared significantly from the blood by hemodialysis or peritoneal dialysis. However, a study indicated that with doses of 400 mg of cefixime, patients undergoing hemodialysis have similar blood profiles as subjects with creatinine clearances of 21 to 60 mL/min.

12.4 Microbiology

Mechanism of Action

As with other cephalosporins, the bactericidal action of cefixime results from inhibition of cell wall synthesis. Cefixime is stable in the presence of certain beta-lactamase enzymes. As a result, certain organisms resistant to penicillins and some cephalosporins due to the presence of beta-lactamases may be susceptible to cefixime.

Resistance

Resistance to cefixime in isolates of Haemophilus influenzaeand Neisseria gonorrhoeaeis most often associated with alterations in penicillin-binding proteins (PBPs). Cefixime may have limited activity against Enterobacteriaceae producing extended spectrum beta-lactamases (ESBLs). Pseudomonasspecies, Enterococcusspecies, strains of Group D streptococci, Listeria monocytogenes,most strains of staphylococci (including methicillin-resistant strains), most strains of Enterobacterspecies, most strains of Bacteroides fragilis,and most strains of Clostridiumspecies are resistant to cefixime.

Antimicrobial Activity

Cefixime has been shown to be active against most isolates of the following microorganisms, both in vitroand in clinical infections [see Indications and Usage (1)].

Gram-positive Bacteria

Streptococcus pneumoniae

Streptococcus pyogenes

Gram-negative Bacteria

Escherichia coli

Haemophilus influenzae

Moraxella catarrhalis

Neisseria gonorrhoeae

Proteus mirabilis

The following in vitrodata are available, but their clinical significance is unknown. At least 90 percent of the following bacteria exhibit an in vitrominimum inhibitory concentration (MIC) less than or equal to the susceptible breakpoint for cefixime against isolates of similar genus or organism group. However, the efficacy of cefixime in treating clinical infections caused by these bacteria has not been established in adequate and well-controlled clinical trials.

Gram-positive Bacteria

Streptococcus agalactiae

Gram-negative Bacteria

Citrobacter amalonaticus

Citrobacter diversus

Haemophilus parainfluenzae

Klebsiella oxytoca

Klebsiella pneumoniae

Pasteurella multocida

Proteus vulgaris

Providenciaspecies

Salmonellaspecies

Serratia marcescens

Shigellaspecies

Susceptibility Testing

For specific information regarding susceptibility test interpretive criteria and associated test methods and quality control standards recognized by FDA for this drug, please see: https://www.fda.gov/STIC.

13 NONCLINICAL TOXICOLOGY

13.1 Carcinogenesis, Mutagenesis, Impairment of Fertility

Lifetime studies in animals to evaluate carcinogenic potential have not been conducted. Cefixime did not cause point mutations in bacteria or mammalian cells, DNA damage, or chromosome damage in vitroand did not exhibit clastogenic potential in vivoin the mouse micronucleus test. In the fertility and reproductive performance study in rats, no difference between control and drug-treated animals was detected in mating behavior, pregnancy rate, or litter parameters (determined at sacrifice on day 13 of pregnancy) at oral doses up to 1000 mg/kg/day (25 times the adult therapeutic dose) administered to males (for 68 days prior to pairing and during the cohabitation period) and females (for 14 days before pairing to weaning).

14 CLINICAL STUDIES

Comparative clinical trials of otitis media were conducted in nearly 400 pediatric patients between the ages of 6 months to 10 years. Streptococcus pneumoniaewas isolated from 47% of the patients, Haemophilus influenzaefrom 34%, Moraxella catarrhalisfrom 15% and S. pyogenesfrom 4%.

The overall response rate of Streptococcus pneumoniaeto cefixime was approximately 10% lower and that of Haemophilus influenzaeor Moraxella catarrhalisapproximately 7% higher (12% when beta-lactamase positive isolates of H. influenzaeare included) than the response rates of these organisms to the active control drugs.

In these studies, patients were randomized and treated with either cefixime at dose regimens of 4 mg/kg twice a day or 8 mg/kg once a day, or with a comparator. Sixty-nine to 70% of the patients in each group had resolution of signs and symptoms of otitis media when evaluated 2 to 4 weeks post-treatment, but persistent effusion was found in 15% of the patients. When evaluated at the completion of therapy, 17% of patients receiving cefixime and 14% of patients receiving effective comparative drugs (18% including those patients who had Haemophilus influenzaeresistant to the control drug and who received the control antibacterial drug) were considered to be treatment failures. By the 2 to 4 week follow-up, a total of 30%-31% of patients had evidence of either treatment failure or recurrent disease.

Table 5. Bacteriological Outcome of Otitis Media
Bacteriological Outcomeof Otitis Mediaat Twoto Four Weeks Post-Therapy Basedon Repeat Middle Ear Fluid Cultureor Extrapolationfrom Clinical Outcome
Organism | Cefixime(a) 4 mg/kg Twice Daily | Cefixime(a) 8 mg/kg Once Daily | Control(a) drugs
Streptococcuspneumoniae | 48/70 (69%) | 18/22 (82%) | 82/100 (82%)
Haemophilusinfluenzaebeta-lactamase negative | 24/34 (71%) | 13/17 (76%) | 23/34 (68%)
Haemophilusinfluenzaebeta-lactamase positive | 17/22 (77%) | 9/12 (75%) | 1/1 (b)
Moraxellacatarrhalis | 26/31 (84%) | 5/5 | 18/24 (75%)
S. pyogenes | 5/5 | 3/3 | 6/7
All Isolates | 120/162 (74%) | 48/59 (81%) | 130/166 (78%)
(a) Number eradicated/number isolated.
(b) An additional 20 beta-lactamase positive isolates of Haemophilusinfluenzaewere isolated, but were excluded from this analysis because they were resistant to the control antibacterial drug. In nineteen of these, the clinical course could be assessed and a favorable outcome occurred in 10. When these cases are included in the overall bacteriological evaluation of therapy with the control drugs, 140/185 (76%) of pathogens were considered to be eradicated.

15 REFERENCES

1. Halperin-Walega, E. Batra VK, Tonelli AP, Barr A, Yacobi A. 'Disposition of Cefixime in the Pregnant and Lactating Rat. Transfer to the Fetus and Nursing Pup'. Drug Metabolism and Disposition.1988:16(1): pp130–134.

16 HOW SUPPLIED/STORAGE AND HANDLING

Cefixime capsules, 400 mg is size "0" capsule with pink opaque cap and pink opaque body, imprinted with "LU" on cap and "U43" on body in black ink, containing white to yellowish white granular powder containing 400 mg of cefixime as the trihydrate and is supplied as follows:

NDC: 70518-3221-00

NDC: 70518-3221-01

NDC: 70518-3221-02

NDC: 70518-3221-03

NDC: 70518-3221-04

NDC: 70518-3221-05

PACKAGING: 2 in 1 BOX

PACKAGING: 1 in 1 POUCH

PACKAGING: 2 in 1 BOX

PACKAGING: 1 in 1 POUCH

PACKAGING: 2 in 1 BOTTLE PLASTIC

PACKAGING: 2 in 1 BOTTLE PLASTIC

Store at 20°C to 25°C (68°F to 77°F) [See USP Controlled Temperature].

Repackaged and Distributed By:

Remedy Repack, Inc.

625 Kolter Dr. Suite #4 Indiana, PA 1-724-465-8762

17 PATIENT COUNSELING INFORMATION

Development of Drug Resistance Bacteria

Patients should be counseled that antibacterial drugs, including cefixime, should only be used to treat bacterial infections. They do not treat viral infections (e.g., the common cold). When cefixime is prescribed to treat a bacterial infection, patients should be told that although it is common to feel better early in the course of therapy, the medication should be taken exactly as directed. Skipping doses or not completing the full course of therapy may: (1) decrease the effectiveness of the immediate treatment and (2) increase the likelihood that bacteria will develop resistance and will not be treatable by cefixime or other antibacterial drugs in the future.

Diarrhea

Advise patients that diarrhea is a common problem caused by antibacterial drugs, including cefixime which usually ends when the antibacterial drug is discontinued. Sometimes after starting treatment with antibacterial drugs, patients can develop watery and bloody stools (with or without stomach cramps and fever) even as late as two or more months after having taken the last dose of the antibacterial drug. If this occurs, patients should contact their physician as soon as possible.

LUPIN and the are registered trademarks of Lupin Pharmaceuticals, Inc.

Repackaged By / Distributed By: RemedyRepack Inc.

625 Kolter Drive, Indiana, PA 15701

(724) 465-8762

PACKAGE LABEL

DRUG: CEFIXIME

GENERIC: CEFIXIME

DOSAGE: CAPSULE

ADMINSTRATION: ORAL

NDC: 70518-3221-0

NDC: 70518-3221-1

NDC: 70518-3221-2

NDC: 70518-3221-3

NDC: 70518-3221-4

NDC: 70518-3221-5

COLOR: pink

SHAPE: CAPSULE

SCORE: No score

SIZE: 22 mm

IMPRINT: LU;U43

PACKAGING: 2 in 1 BOX

PACKAGING: 1 in 1 POUCH

PACKAGING: 2 in 1 BOX

PACKAGING: 1 in 1 POUCH

PACKAGING: 2 in 1 BOTTLE PLASTIC

PACKAGING: 2 in 1 BOTTLE PLASTIC

ACTIVE INGREDIENT(S):

- CEFIXIME 400mg in 1

INACTIVE INGREDIENT(S):

- CROSCARMELLOSE SODIUM
- FERRIC OXIDE RED
- FERROSOFERRIC OXIDE
- GELATIN
- HYDROXYPROPYL CELLULOSE, LOW SUBSTITUTED
- MAGNESIUM STEARATE
- MANNITOL
- POTASSIUM HYDROXIDE
- PROPYLENE GLYCOL
- SHELLAC
- SILICON DIOXIDE
- SODIUM LAURYL SULFATE
- TITANIUM DIOXIDE